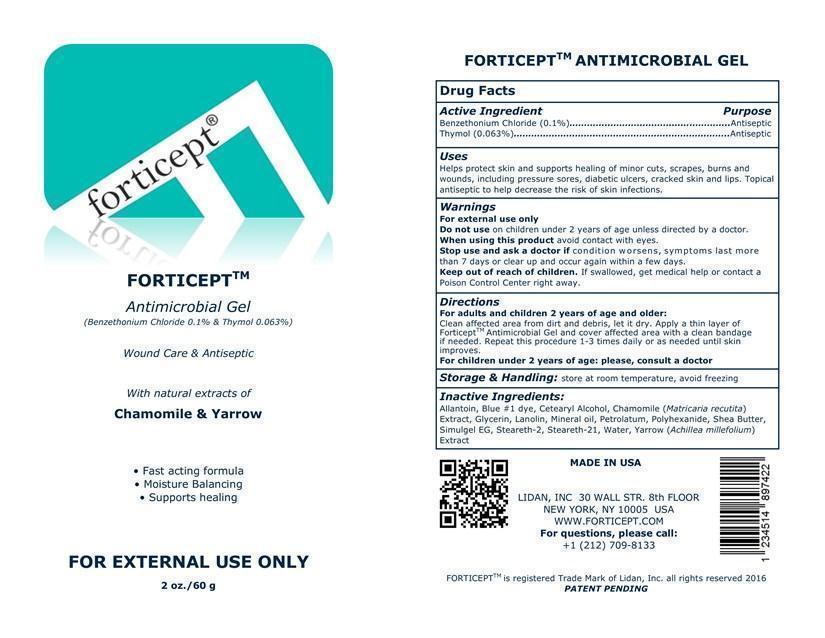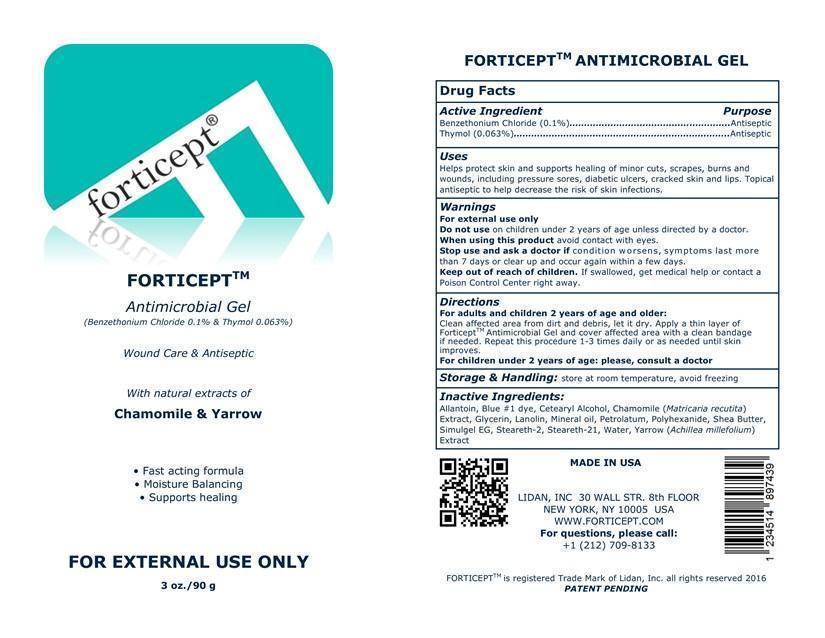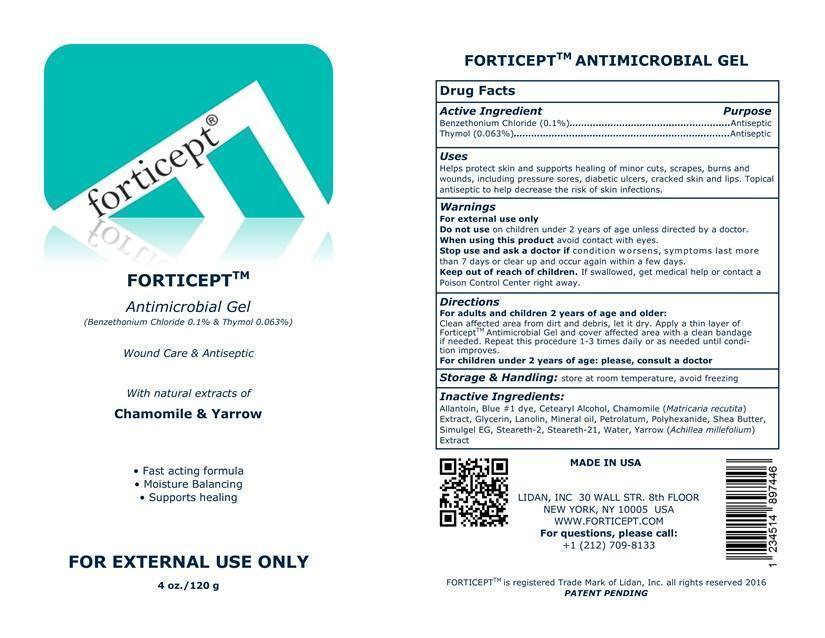 DRUG LABEL: Forticept Antimicrobial Gel
NDC: 52261-0701 | Form: Gel
Manufacturer: Cosco International, Inc.
Category: otc | Type: HUMAN OTC DRUG LABEL
Date: 20161027

ACTIVE INGREDIENTS: benzethonium chloride 1 g/1000 g; thymol 1 g/1000 g
INACTIVE INGREDIENTS: allantoin 2 g/1000 g; fd&c blue no. 1 0.009 g/1000 g; CETOSTEARYL ALCOHOL 2.8 g/1000 g; chamomile .1 g/1000 g; glycerin 20 g/1000 g; isohexadecane 3 g/1000 g; LANOLIN 1.2 g/1000 g; mineral oil 1.6 g/1000 g; petrolatum 3.6 g/1000 g; polihexanide 2 g/1000 g; polysorbate 80 0.5 g/1000 g; shea butter .8 g/1000 g; sodium acrylate/sodium acryloyldimethyltaurate copolymer (4000000 MW) 6.5 g/1000 g; STEARETH-2 1.2 g/1000 g; STEARETH-21 1.2 g/1000 g; water 951.591 g/1000 g; ACHILLEA MILLEFOLIUM .1 g/1000 g

Drug Facts

Active Ingredient/Purpose

Benzethonium Chloride............Antiseptic

Thymol................................Antiseptic

Uses

Helps protect skin and supports healing of minor cuts, scrapes, burns and wounds, including pressure sores, diabetic ulcers, cracked skin and lips. Topical antiseptic to help decrease the risk of skin infections.

Warnings For external use only.

Do not use on children under 2 years of age unless directed by a doctor.

When using this product avoid contact with eyes.

Stop use and ask a doctor if condition worsens, symptoms last more than 7 days or clear up and occur again within a few days.

Keep out of reach of children. If swallowed, get medical help or contact a Poison Control Center right away

Directions:

Adults and children 2 years of age and older:

Clean affected area from dirt and debris, let it dry. Apply a thin layer of ForticeptTM Antimicrobial Gel and cover affected area with a clean bandage if needed. Repeat this procedure 1-3 times daily or as needed until condition improves.

Children under 2 years of age: please, consult a doctor

Storage and handling:

Store at room temperature, avoid freezing

Inactive ingredients:

Allantoin, Blue #1 dye, Cetearyl Alcohol, Chamomile (Matricaria recutita) Extract, Glycerin, Lanolin, Mineral oil, Petrolatum, Polyhexanide, Shea Butter, Simulgel EG, Steareth-2, Steareth-21, Water, Yarrow (Achillea millefolium) Extract